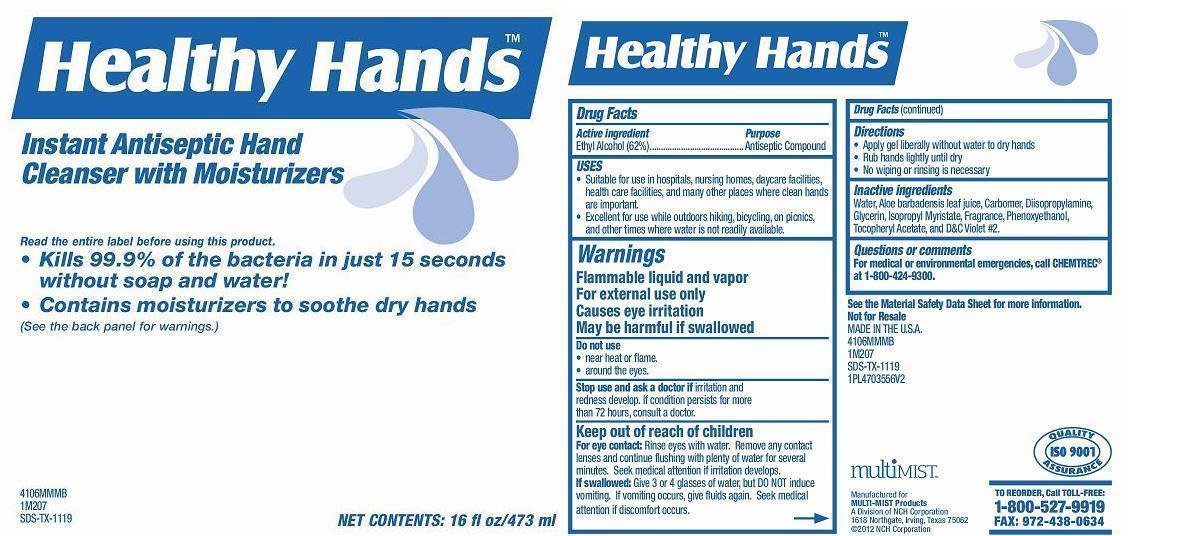 DRUG LABEL: HEALTHY HANDS INSTANT ANTISEPTIC HAND CLEANSER WITH MOISTURIZERS
NDC: 55533-556 | Form: SOAP
Manufacturer: NCH Corporation
Category: otc | Type: HUMAN OTC DRUG LABEL
Date: 20131015

ACTIVE INGREDIENTS: ALCOHOL 0.62 mL/1 mL
INACTIVE INGREDIENTS: WATER; CARBOMER HOMOPOLYMER TYPE C (ALLYL PENTAERYTHRITOL CROSSLINKED); GLYCERIN; ALOE VERA LEAF; ISOPROPYL MYRISTATE; PHENOXYETHANOL; .ALPHA.-TOCOPHEROL ACETATE; DIISOPROPYLAMINE

Active ingredient

Ethyl Alcohol 62 % w/w

Purpose

Antiseptic Compound

Keep out of reach of children

For eye contact: Rinse eyes with water. Remove any contact lenses and continue flushing with plenty of water for several minutes. Seek medical attention if irritation develops.

If swallowed: Give 3 or 4 glasses of water, but DO NOT induce vomiting. If vomiting occurs, give fluids again. Seek medical attention if discomfort occurs.

Uses

• Suitable for use in hospitals, nursing homes, daycare facilities, health care facilities, and many other places where clean hands are important.

• Excellent for use while outdoors hiking, bicycling, on picnics, and other times where water is not readily available.

Warnings Flammable liquid and vapor For external use only Causes eye irritation May be harmful if swallowed

Do not use

• near heat or flame.

• around the eyes.

Stop use and ask a doctor if irritation and redness develop. If condition persists for more than 72 hours, consult a doctor.

Directions

• Apply gel liberally without water to dry hands

• Rub hands lightly until dry

• No wiping or rinsing is necessary

Inactive ingredients:

Water, Aloe barbadensis leaf juice, Carbomer, Diisopropylamine, Glycerin, Isopropyl Myristate, Fragrance, Phenoxyethanol, Tocopheryl Acetate, and D&C Violet #2.